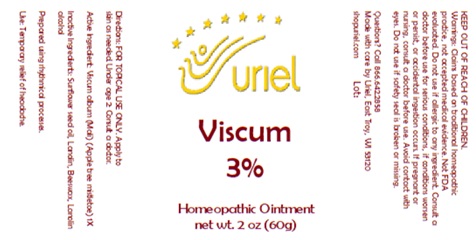 DRUG LABEL: Viscum 3%
NDC: 48951-9393 | Form: OINTMENT
Manufacturer: Uriel Pharmacy, Inc
Category: homeopathic | Type: HUMAN OTC DRUG LABEL
Date: 20260112

ACTIVE INGREDIENTS: VISCUM ALBUM FRUITING TOP 1 [hp_X]/1 g
INACTIVE INGREDIENTS: SUNFLOWER OIL; LANOLIN ALCOHOL; BEESWAX; LANOLIN

Viscum 3

INDICATIONS AND USAGE

Directions: FOR TOPICAL USE ONLY.

DOSAGE AND ADMINISTRATION

Apply to skin as needed. Under age 2: Consult a doctor.

Active Ingredient: Viscum album (Mali) (Apple tree mistletoe) 1X

INACTIVE INGREDIENT

Inactive Ingredients: Sunflower seed oil, Lanolin, Beeswax, Lanolin alcohol

Prepared using rhythmical processes.

PURPOSE

Use: Temporary relief of headache.

KEEP OUT OF REACH OF CHILDREN.

WARNINGS

Warnings: Claims based on traditional homeopathic practice, not accepted medical evidence. Not FDA evaluated. Do not use if allergic to any ingredient. Consult a doctor before use for serious conditions, if conditions worsen or persist, or accidental ingestion occurs. If pregnant or nursing, consult a doctor before use. Avoid contact with eyes. Do not use if safety seal is broken or missing.

Questions? Call 866.642.2858
Made with care by Uriel, East Troy, WI 53120
shopuriel.com Lot: